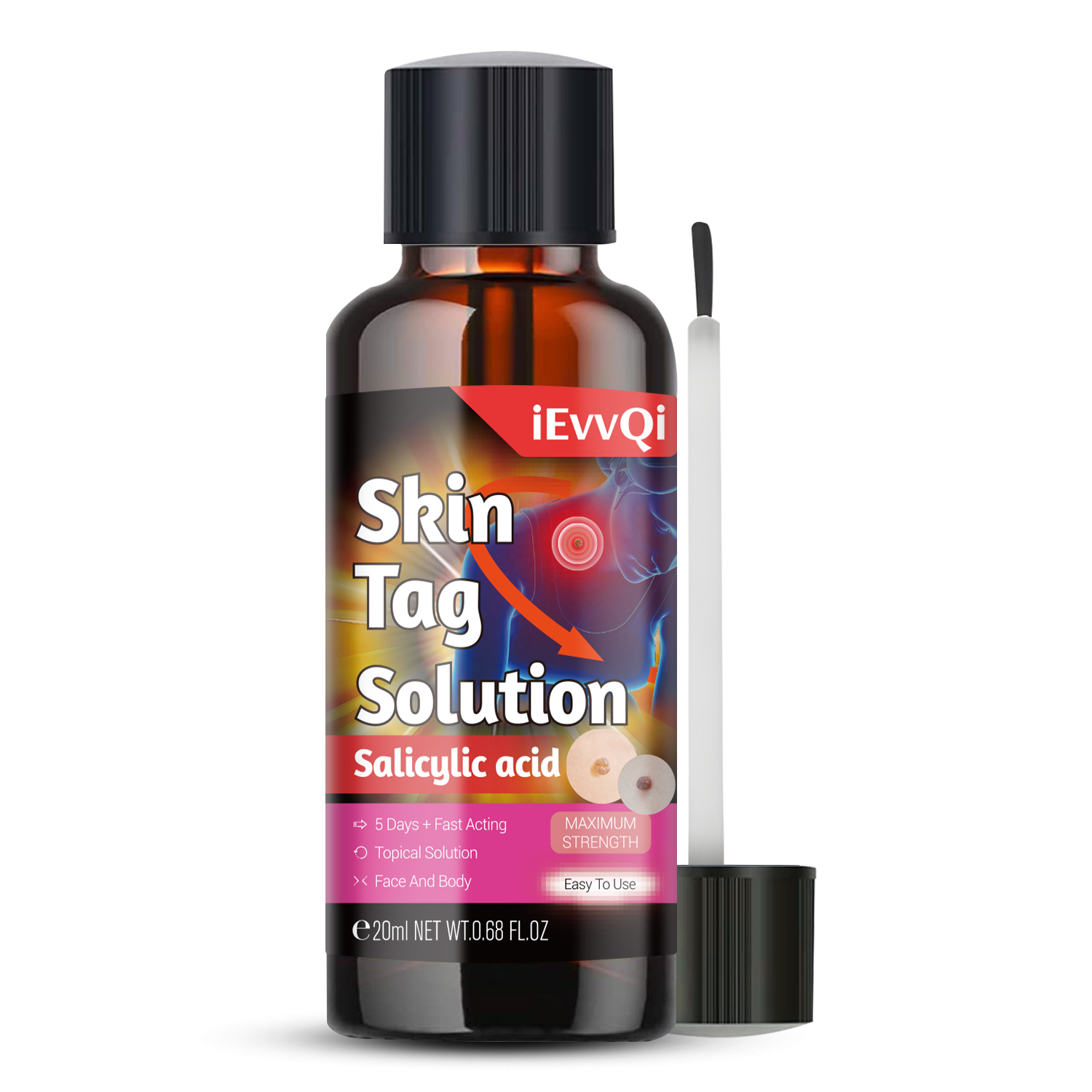 DRUG LABEL: Skin Tag Solution
NDC: 84117-027 | Form: LIQUID
Manufacturer: Shenzhen Hengkaifeng Commerce and Trade Co., Ltd
Category: otc | Type: HUMAN OTC DRUG LABEL
Date: 20241006

ACTIVE INGREDIENTS: SALICYLIC ACID 5 g/100 mL
INACTIVE INGREDIENTS: WATER

ACTIVE INGREDIENT

Salicylic acid

Purpose

Skin Tag Solution

Use

Skin Tag Solution

Warnings

For adult external use only. Flammable.
Keep away from heat or flame
Do not use
* Pregnant women and children.
* on open skin wounds

Keep Out Of Reach Of Children

Directions Of Safe Use:

* 1-2 times per day.

Other information

Store between15-30C(59-86F)
Avoid freezing and excessive heat above
40C (104F)

Inactive ingredients

water